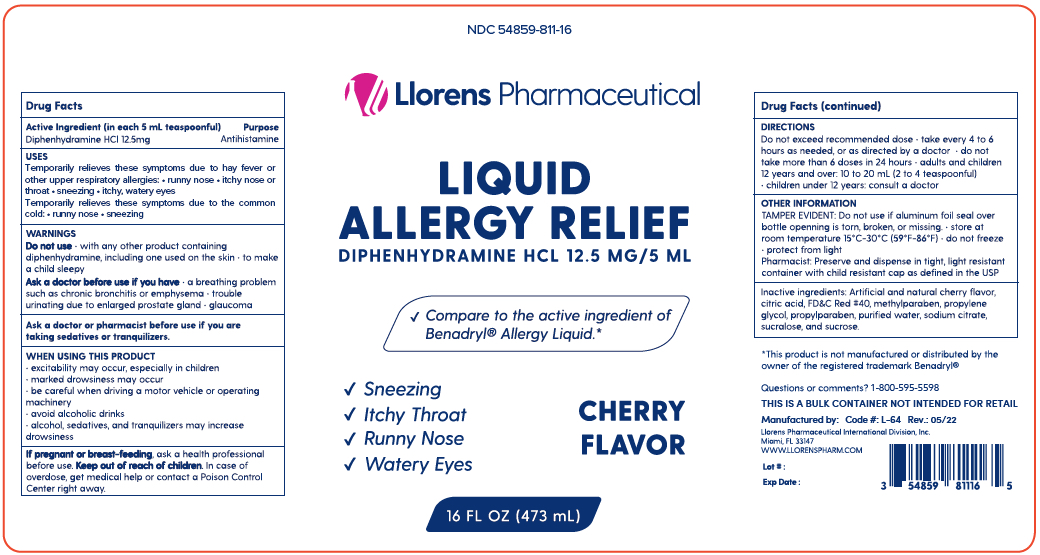 DRUG LABEL: Allergy Relief
NDC: 54859-811 | Form: LIQUID
Manufacturer: LLORENS PHARMACEUTICALS INTERNATIONAL DIVISION
Category: otc | Type: HUMAN OTC DRUG LABEL
Date: 20251231

ACTIVE INGREDIENTS: DIPHENHYDRAMINE HYDROCHLORIDE 12.5 mg/5 mL
INACTIVE INGREDIENTS: ANHYDROUS CITRIC ACID; FD&C RED NO. 40; METHYLPARABEN; PROPYLENE GLYCOL; PROPYLPARABEN; WATER; SODIUM CITRATE; SUCRALOSE; SUCROSE

Llorens - Allergy Relief 811

Active ingredient (in each 5 mL teaspoonful)

Diphenhydramine HCl 12.5 mg

Purpose

Antihistamine

Uses

- Temporarily relieves these symptoms of hay fever or other upper respiratory allergies:
- runny nose
- itchy nose or throat
- sneezing
- itchy, watery eyes
- Temporarily relieves these symptoms due to the common cold:
- runny nose
- sneezing

Warnings

Do not use

- with any other product conatining diphenhydramine, including one used on the skin
- to make a child sleepy

Ask a doctor before use if you have

- a breathing problem such as chronic bronchitis or emphysema
- trouble urinating due to enlarged prostate gland
- glaucoma

Ask a doctor or pharmacist before use if you are

taking sedatives or tranquilizers.

When using this product

- excitability may occur, especially in children
- marked drowsiness may occur
- be careful when driving motor vehicle or operating machinery
- avoid alcoholic drinks
- alcohol, sedatives, and tranquilizers may increase drowsiness

PREGNANCY OR BREAST FEEDING

If pregnant or breast-feeding, ask a health professional before use.

Keep out of reach of children. In case of overdose, get medical help or contact a Poison Control Center right away.

Directions

- do not exceed recommended dose
- take every 4 to 6 hours as needed, or as directed by a doctor
- do not take more than 6 doses in 24 hours
- adults and children 12 years and over: 10 to 20 mL (2 to 4 teaspoonful)
- children under 12 years: consult a doctor

INACTIVE INGREDIENT

Inactive ingredients: Artificial and natural cherry flavor, citric acid, FD&C #40, methylparaben, propylene glycol, propylparaben, purified water, sodium citrate, sucralose and sucrose.

Questions or comments? 1-800-540-3765